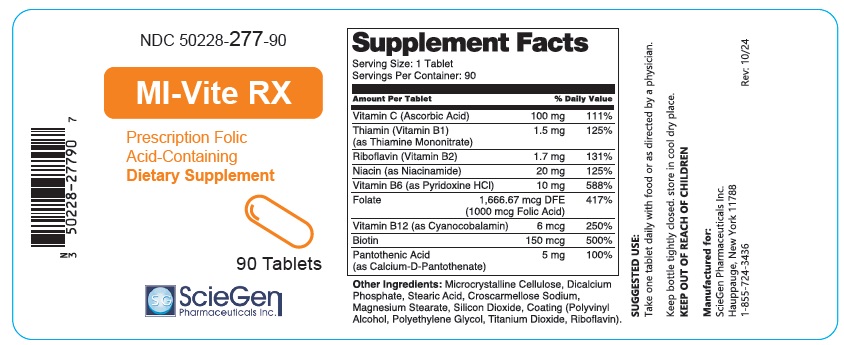 DRUG LABEL: MI-Vite RX
NDC: 50228-277 | Form: TABLET
Manufacturer: ScieGen Pharmaceuticals, Inc
Category: other | Type: DIETARY SUPPLEMENT
Date: 20241030

ACTIVE INGREDIENTS: ASCORBIC ACID 100 mg/1 1; THIAMINE MONONITRATE 1.5 mg/1 1; RIBOFLAVIN 1.7 mg/1 1; NIACINAMIDE 20 mg/1 1; PYRIDOXINE HYDROCHLORIDE 10 mg/1 1; FOLIC ACID 1666.67 ug/1 1; CYANOCOBALAMIN 6 ug/1 1; BIOTIN 150 ug/1 1; PANTOTHENIC ACID 5 mg/1 1
INACTIVE INGREDIENTS: MICROCRYSTALLINE CELLULOSE; DICALCIUM PHOSPHATE; STEARIC ACID; CROSCARMELLOSE SODIUM; MAGNESIUM STEARATE; SILICON DIOXIDE; POLYVINYL ALCOHOL; POLYETHYLENE GLYCOL, UNSPECIFIED; TITANIUM DIOXIDE

MI-Vite RX

HEALTH CLAIM

NDC 50228-277-90

MI-Vite RX

Prescription Folic
Acid-Containing
Dietary Supplement

DOSAGE AND ADMINISTRATION

Supplement Facts
Serving Size: 1 Tablet
Servings Per Container: 90
Amount Per Tablet |  | % Daily Value
Vitamin C (Ascorbic Acid) | 100mg | 111%
Thiamin (Vitamin B1) (as Thiamine Mononitrate) | 1.5 mg | 125%
Riboflavin (Vitamin B2) | 1.7 mg | 131%
Niacin (as Niacinamide) | 20 mg | 125%
Vitamin B6 (as Pyridoxine HCI) | 10 mg | 588%
Folate | 1,666.67 mcg DFE (1000 mcg Folic Acid) | 417%
Vitamin B12 (as Cyanocobalamin) | 6 mcg | 250%
Biotin | 150 mcg | 500%
Pantothenic Acid (as Calcium-D-Pantothenate) | 5mg | 100%

Other Ingredients: Microcrystalline Cellulose, Dicalcium Phosphate, Stearic Acid, Croscarmellose Sodium, Magnesium Stearate, Silicon Dioxide, Coating (Polyvinyl Alcohol, Polyethylene Glycol, Titanium Dioxide, Riboflavin).

SUGGESTED USE:
Take one tablet daily with food or as directed by a physician.

Keep bottle tightly closed. store in cool dry place.
KEEP OUT OF REACH OF CHILDREN

Manufactured for:
ScieGen Pharmaceuticals Inc.
Hauppauge, New York 11788
1-855-724-3436

Rev: 10/24

PRINCIPAL DISPLAY PANEL - 90 Tablet Bottle Label

NDC 50228-277-90

MI-Vite RX

Prescription Folic
Acid-Containing
Dietary Supplement

90 Tablets

ScieGen
Pharmaceuticals Inc.